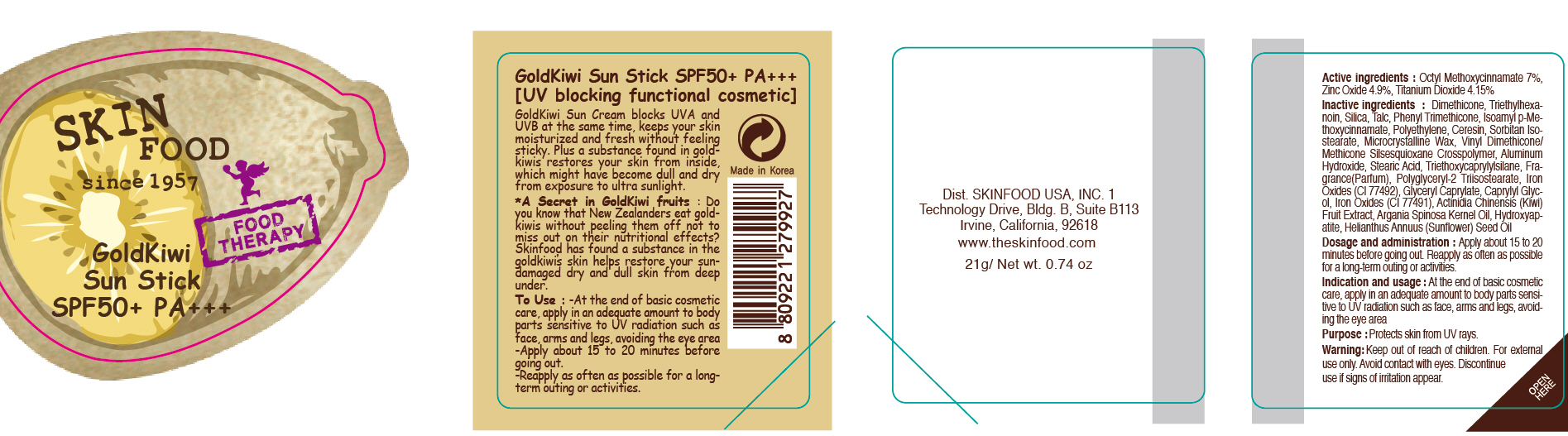 DRUG LABEL: GOLDKIWI SUN
NDC: 76214-039 | Form: STICK
Manufacturer: SKINFOOD CO., LTD.
Category: otc | Type: HUMAN OTC DRUG LABEL
Date: 20111009

ACTIVE INGREDIENTS: OCTINOXATE 1.47 g/21 g; ZINC OXIDE 1.03 g/21 g; TITANIUM DIOXIDE 0.87 g/21 g
INACTIVE INGREDIENTS: DIMETHICONE; TRIETHYLHEXANOIN; SILICON DIOXIDE; TALC; PHENYL TRIMETHICONE; CERESIN; ALUMINUM HYDROXIDE; STEARIC ACID; TRIETHOXYCAPRYLYLSILANE; GLYCERYL CAPRYLATE; CAPRYLYL GLYCOL; KIWI FRUIT; ARGAN OIL; SUNFLOWER OIL

Drug Facts

ACTIVE INGREDIENT

Active ingredients: OCTINOXATE 7%, ZINC OXIDE 4.9%, TITANIUM DIOXIDE 4.15%

Inactive ingredients:
Dimethicone, Triethylhexanoin, Silica, Talc, Phenyl Trimethicone, Isoamyl p-Methoxycinnamate, Polyethylene, Ceresin, Sorbitan Isostearate, Microcrystalline Wax, Vinyl Dimethicone/Methicone Silsesquiox ane Crosspolymer, Aluminum Hydroxide, Stearic Acid, Triethoxycaprylylsilane, Fragrance(Parfum), Polyglyceryl-2 Triisostearate, Iron Oxides (CI 77492), Glyceryl Caprylate, Caprylyl Glycol, Iron Oxides (CI 77491), Actinidia Chinensis (Kiwi) Fruit Extract, Argania Spinosa Kernel Oil, Hydroxyapatite, Helianthus Annuus (Sunflower) Seed Oil

Purpose: Protects skin from UV rays.

Warnings:
For external use only.
Avoid contact with eyes.
Discontinue use if signs of irritation appear.

Keep out of reach of children:
Keep out of reach of children.

Indication and usage:
At the end of basic cosmetic care, apply in an adequate amount to body parts sensitive to UV radiation such as face, arms and legs, avoiding the eye area

Dosage and administration:
Apply about 15 to 20 minutes before going out.
Reapply as often as possible for a long-term outing or activities.